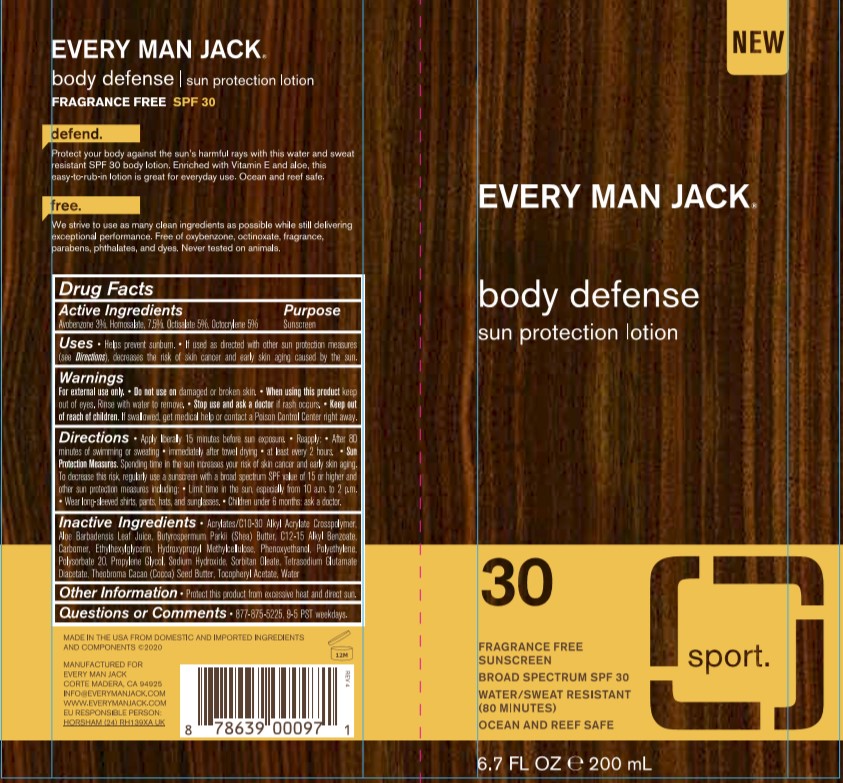 DRUG LABEL: Every Man Jack
NDC: 58443-0360 | Form: LOTION
Manufacturer: Prime Enterprises Inc.
Category: otc | Type: HUMAN OTC DRUG LABEL
Date: 20200921

ACTIVE INGREDIENTS: HOMOSALATE 75.75 mg/1 mL; OCTOCRYLENE 50.5 mg/1 mL; AVOBENZONE 30.3 mg/1 mL; OCTISALATE 50.5 mg/1 mL
INACTIVE INGREDIENTS: ETHYLHEXYLGLYCERIN; SORBITAN MONOOLEATE; CARBOMER HOMOPOLYMER, UNSPECIFIED TYPE; COCOA BUTTER; HIGH DENSITY POLYETHYLENE; PHENOXYETHANOL; ALKYL (C12-15) BENZOATE; POLYSORBATE 20; ALPHA-TOCOPHEROL ACETATE; WATER; ALOE VERA LEAF; SODIUM HYDROXIDE; HYPROMELLOSE, UNSPECIFIED; PROPYLENE GLYCOL; TETRASODIUM GLUTAMATE DIACETATE; CARBOMER INTERPOLYMER TYPE A (ALLYL SUCROSE CROSSLINKED); SHEA BUTTER

Every Man Jack SPF 30 Body Lotion

Active Ingredients

Avobenzone 3%

Octocrylene 5%

Homosalate 7.5%

Octisalate 5%

INACTIVE INGREDIENTS

Acrylates/C10-30 Alkyl Acrylate Crosspolymer, Aloe Barbadensis Leaf Juice, Butyrospermum Parkii (Shea) Butter, C12-15 Alkyl Benzoate, Carbomer, Ethylhexylglycerin, Hydroxypropyl Methylcellulose, Phenoxyethanol, Polyethylene, Polysorbate 20, Propylene Glycol, Sodium Hydroxide, Sorbitan Oleate, Tetrasodium Glutamate Diacetate, Theobroma Cacao (Cocoa) Seed Butter, Tocopheryl Acetate, Water

Uses

- helps prevent sunburn
  - if used as directed with other sun protection measures (see Directions) decreases the risk of skin cancer and early skin aging caused by the sun

Warnings

For external use only

Do not use on damaged or broken skin.

When using this product keep out of eyes. Rinse with water to remove.

Stop use and ask a doctor if rash occurs.

Keep out of reach of children. If product is swallowed, get medical help or contact a Poison Control Center right away.

Do not use on damaged or broken skin

When using this product keep out of eyes. Rinse with water to remove.

Stop use and ask a doctor if rash occurs

Keep out of reach of children. If product is swallowed, get medical help or contact a Poison Control Center right away.

Purpose

Sunscreen

Directions

- apply liberally 15 minutes before sun exposure
- reapply:
- after 80 minutes of swimming or sweating
- immediately after towel drying
- at least every 2 hours
- Sun Protection Measures Spending time in the sun increases your risk of skin cancer and early skin aging. To decrease this risk, regularly use a sunscreen with a broad spectrum SPF value of 15 or higher and other sun protection measures including:
- limit time in the sun, especially from 10am-2pm
- wear long sleeve shirts, pants, hats, and sunglasses
- children under 6 months: Ask a doctor

Other Information

- protect this product from excesive heat and direct sun

Questions or Comments?

877-875-5225, 9-5 PST weekdays.